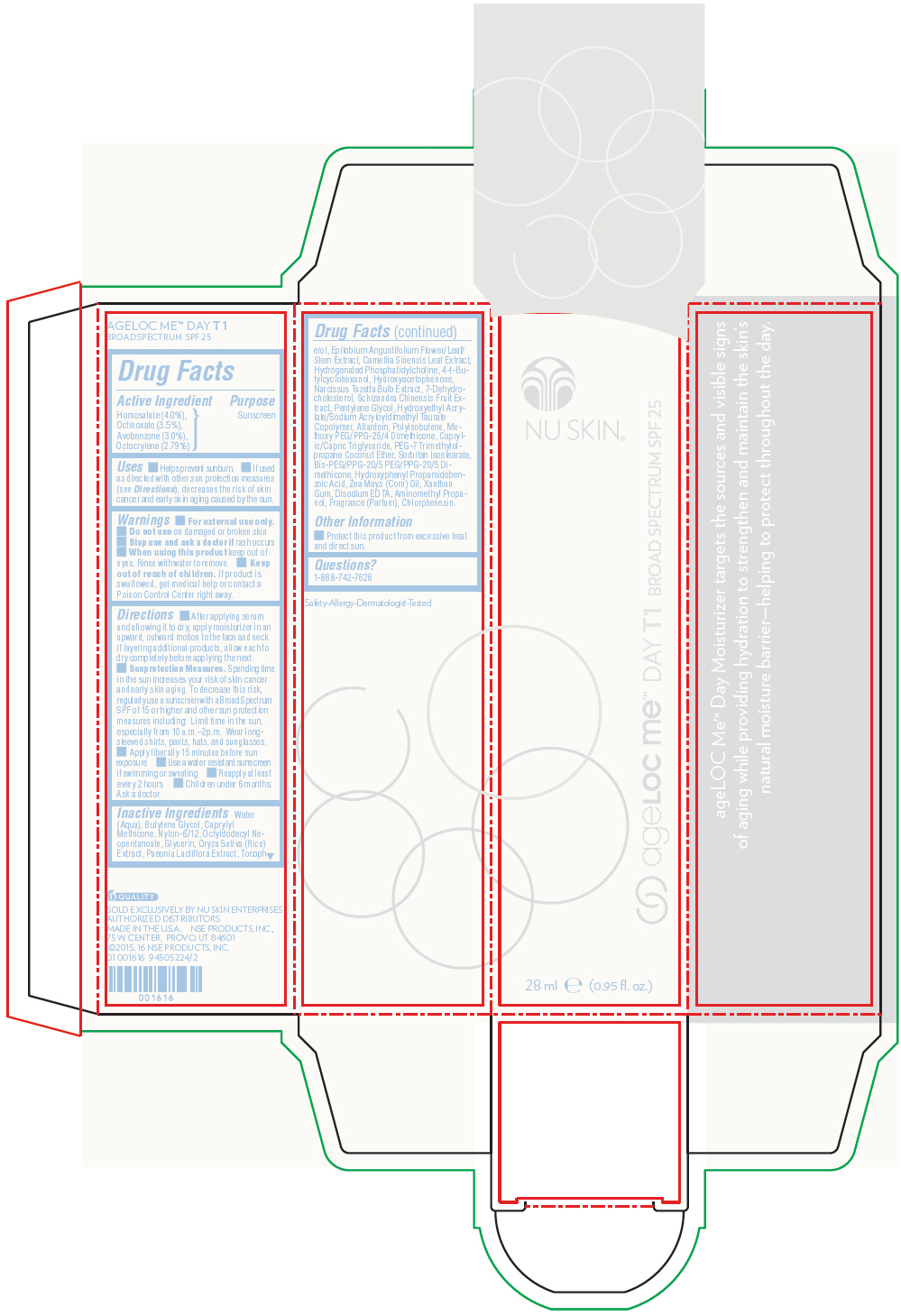 DRUG LABEL: Nu Skin ageLOC Me Day T1 Broad Spectrum SPF 25
NDC: 62839-1616 | Form: LOTION
Manufacturer: NSE Products, Inc.
Category: otc | Type: HUMAN OTC DRUG LABEL
Date: 20191226

ACTIVE INGREDIENTS: Homosalate 40 mg/1 mL; Octinoxate 35 mg/1 mL; Avobenzone 30 mg/1 mL; Octocrylene 27.9 mg/1 mL
INACTIVE INGREDIENTS: Water; Butylene Glycol; Octyldodecyl Neopentanoate; Caprylyl Trisiloxane; Pentylene Glycol; Glycerin; Medium-Chain Triglycerides; Rice Germ; Xanthan Gum; 4-Tert-Butylcyclohexanol; Chlorphenesin; Allantoin; Edetate Disodium; Epilobium Angustifolium Flowering Top; Green Tea Leaf; Sorbitan Isostearate; Hydroxyphenyl Propamidobenzoic Acid; Schisandra Chinensis Fruit; Corn Oil; Narcissus Tazetta Bulb; 7-Dehydrocholesterol; Aminomethylpropanol; Tocopherol

Nu Skin® ageLOC Me™ Day T1 Broad Spectrum SPF 25

Drug Facts

Active Ingredient

Homosalate (4.0%),
Octinoxate (3.5%),
Avobenzone (3.0%),
Octocrylene (2.79%)

Purpose

Sunscreen

Uses

- Helps prevent sunburn.
- If used as directed with other sun protection measures (see Directions), decreases the risk of skin cancer and early skin aging caused by the sun.

Warnings

- For external use only.

- Do not use on damaged or broken skin

- Stop use and ask a doctor if rash occurs

- When using this product keep out of eyes. Rinse with water to remove.

- Keep out of reach of children. If product is swallowed, get medical help or contact a Poison Control Center right away.

Directions

- After applying serum and allowing it to dry, apply moisturizer in an upward, outward motion to the face and neck. If layering additional products, allow each to dry completely before applying the next.
- Sunprotection Measures. Spending time in the sun increases your risk of skin cancer and early skin aging. To decrease this risk, regularly use a sunscreen with a Broad Spectrum SPF of 15 or higher and other sun protection measures including: Limit time in the sun, especially from 10 a.m.–2p.m. Wear long-sleeved shirts, pants, hats, and sunglasses.
- Apply liberally 15 minutes before sun exposure
- Use a water resistant sunscreen if swimming or sweating
- Reapply at least every 2 hours
- Children under 6 months: Ask a doctor

Inactive Ingredients

Water (Aqua), Butylene Glycol, Caprylyl Methicone, Nylon-6/12, Octyldodecyl Neopentanoate, Glycerin, Oryza Sativa (Rice) Extract, Paeonia Lactiflora Extract, Tocopherol, Epilobium Angustifolium Flower/Leaf/Stem Extract, Camellia Sinensis Leaf Extract, Hydrogenated Phosphatidylcholine, 4-t-Butylcyclohexanol, Hydroxyacetophenone, Narcissus Tazetta Bulb Extract, 7-Dehydrocholesterol, Schizandra Chinensis Fruit Extract, Pentylene Glycol, Hydroxyethyl Acrylate/Sodium Acryloyldimethyl Taurate Copolymer, Allantoin, Polyisobutene, Methoxy PEG/PPG-25/4 Dimethicone, Caprylic/Capric Triglyceride, PEG-7 Trimethylolpropane Coconut Ether, Sorbitan Isostearate, Bis-PEG/PPG-20/5 PEG/PPG-20/5 Dimethicone, Hydroxyphenyl Propamidobenzoic Acid, Zea Mays (Corn) Oil, Xanthan Gum, Disodium EDTA, Aminomethyl Propanol, Fragrance (Parfum), Chlorphenesin.

Other Information

- Protect this product from excessive heat and direct sun.

Questions?

1-888-742-7626

PRINCIPAL DISPLAY PANEL - 28 ml Cartridge Carton

NU SKIN®

ageLOC me™ DAY T1 BROAD SPECTRUM SPF 25

28 ml e (0.95 fl. oz.)